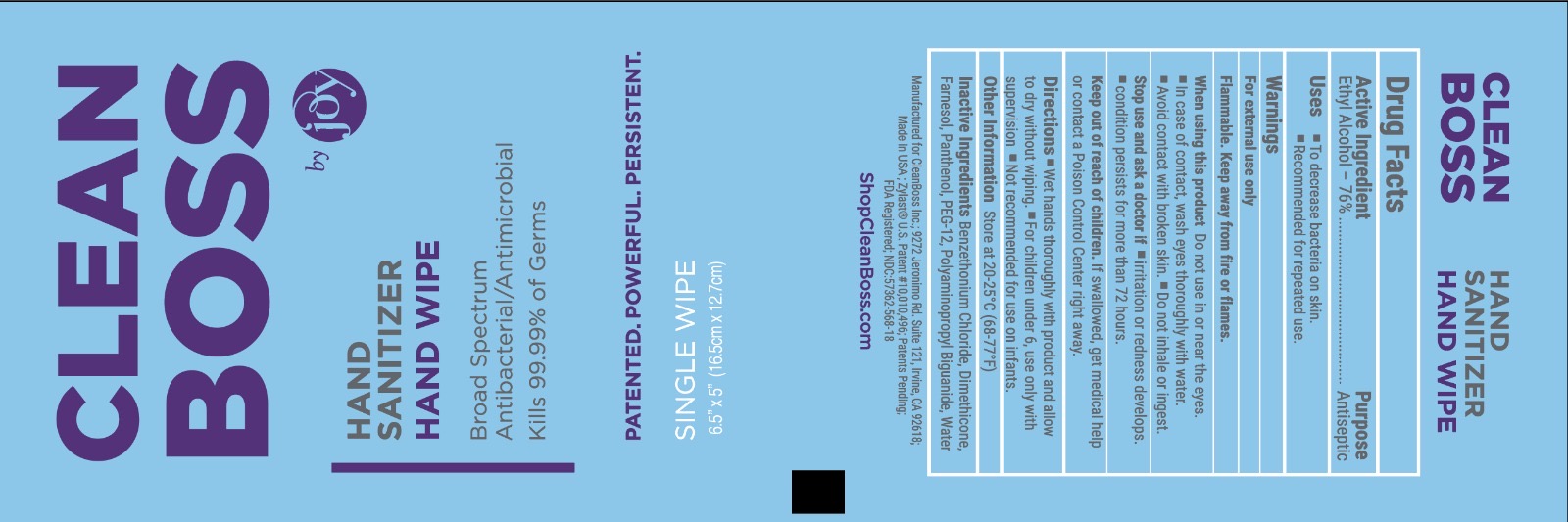 DRUG LABEL: Hand Sanitizing Wipes
NDC: 57362-568 | Form: SWAB
Manufacturer: Innovative Biodefense
Category: otc | Type: HUMAN OTC DRUG LABEL
Date: 20230916

ACTIVE INGREDIENTS: ALCOHOL 76 mL/100 mL
INACTIVE INGREDIENTS: WATER

CleanBoss
Individually Wrapped Hand Sanitizer Hand Wipes

ACTIVE INGREDIENT

Ethyl Alcohol - 76%

PURPOSE

Antiseptic

INDICATIONS AND USAGE

- To decrease bacteria on skin.
- Recommended for repeated use.

WARNINGS

For external use only.

Flammable. Keep away from flames or fires.

- Do not use in or near eyes.
- In case of contact, wash eyes thoroughly with water.
- Avoid contact with broken skin.
- Do not inhale or ingest.

STOP USE

- Irritation or redness develops.
- Condition persists for more than 72 hours.

KEEP OUT OF REACH OF CHILDREN

If swallowed, get medical help or call a Poison Control Center right away.

DOSAGE AND ADMINISTRATION

- Wet hands thoroughly with product and let dry without wiping.
- For children under 6, use only with adult supervision.
- Not recommended for use on infants.

STORAGE AND HANDLING

store 20-25*C (66-77*F)

INACTIVE INGREDIENT

Benzethonium Chloride, Dimethicone, Farnesol, Panthenol, PEG-12, Polyaminopropyl Biguanide

PACKAGE LABEL

CleanBoss

Hand Sanitizer

Hand Wipe

Patented.Powerful.Persistent

NDC: 57362-568-18